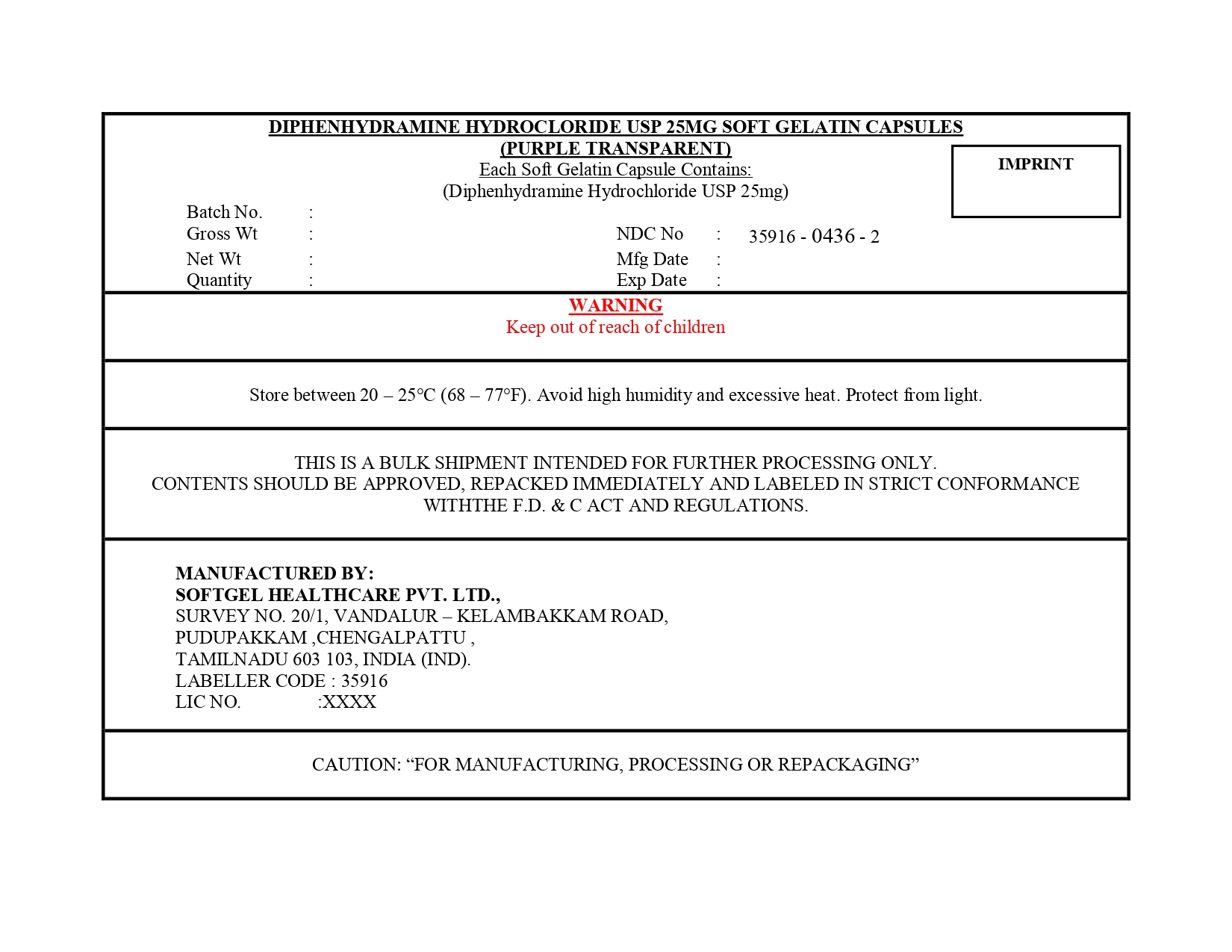 DRUG LABEL: DIPHENHYDRAMINE HYDROCHLORIDE
NDC: 35916-0436 | Form: CAPSULE, LIQUID FILLED
Manufacturer: SOFTGEL HEALTHCARE PRIVATE LIMITED
Category: otc | Type: HUMAN OTC DRUG LABEL
Date: 20260127

ACTIVE INGREDIENTS: DIPHENHYDRAMINE HYDROCHLORIDE 25 mg/1 1
INACTIVE INGREDIENTS: GELATIN; GLYCERIN; POLYETHYLENE GLYCOL 400; PROPYLENE GLYCOL; SORBITOL; WATER; FD&C RED NO. 40; FD&C BLUE NO. 1

Diphenhydramine Hydrochloride Capsules, USP 25 mg (Purple Transparent)

Active ingredient (in each softgel)

Diphenhydramine Hydrochloride USP 25mg

Purpose

Antihistamine

Uses

- temporarily relieves these symptoms due to hay fever or other upper respiratory allergies:
- runny nose
- sneezing
- itchy, watery eyes
- itching of the nose or throat
- temporarily relieves these symptoms due to the common cold:
- runny nose
- sneezing

Warnings

Do not use

- to make a child sleepy
- with any other product containing diphenhydramine, even one used on skin

Ask a Doctor before use if you have

- a breathing problem such as emphysema or chronic bronchitis
- glaucoma
- trouble urinating due to an enlarged prostate gland

Ask a Doctor or Pharmacist before use if you are taking sedatives or tranquilizers

When using this product

- marked drowsiness may occur
- avoid alcoholic drinks
- alcohol, sedatives and tranquilizers may increase drowsiness
- be careful when driving a motor vehicle or operating machinery
- excitability may occur, especially in children

PREGNANCY OR BREAST FEEDING

If pregnant or breast-feeding, ask a health professional before use.

Keep out of reach of children. In case of overdose, get medical help or contact a Poison Control Center right away.

Directions

- take every 4 to 6 hours
- do not take more than 6 doses in 24 hours

adults and children 12 years and over | 1 to 2 capsules
children 6 to under 12 years | 1 capsule
children under 6 years | do not use this product in children under 6 years of age

Other Information

- store between 20° to 25°C (68° to 77°F). Avoid high humidity and excessive heat. Protect from light.
- do not use if carton is open or blister unit is broken

Inactive Ingredients

FD & C blue no.1, FD & C red no.40, gelatin, glycerin, polyethylene glycol 400, propylene glycol, purified water, sorbitol sorbitan solution